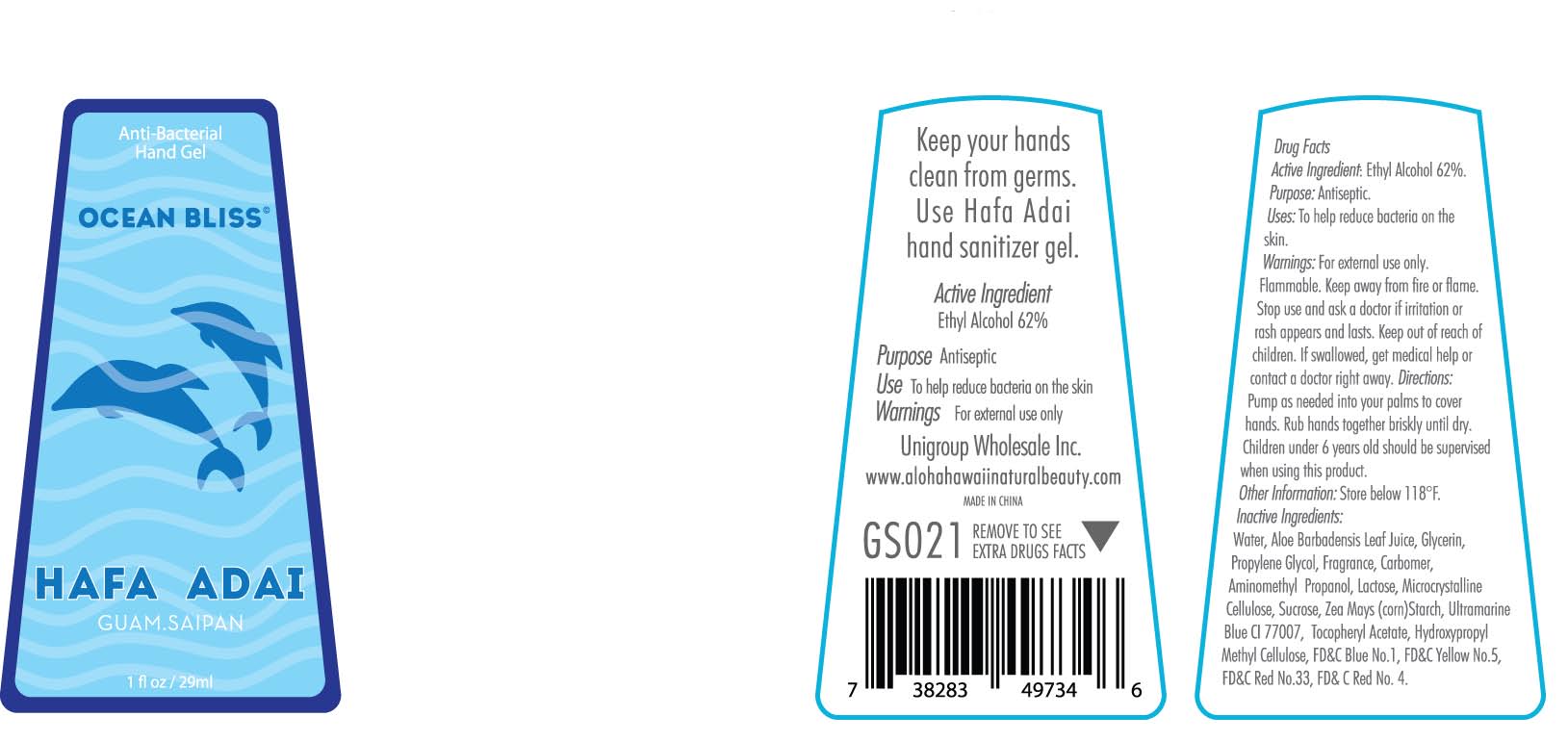 DRUG LABEL: anti-bacterial hand gel
NDC: 69358-0020 | Form: GEL
Manufacturer: UniGroup Wholesale Inc.
Category: otc | Type: HUMAN OTC DRUG LABEL
Date: 20160324

ACTIVE INGREDIENTS: ALCOHOL 62 mL/100 mL
INACTIVE INGREDIENTS: WATER; ALOE VERA LEAF; GLYCERIN; PROPYLENE GLYCOL; CARBOMER INTERPOLYMER TYPE A (55000 CPS); ULTRAMARINE BLUE; AMINOMETHYL PROPANEDIOL; LACTOSE; CELLULOSE, MICROCRYSTALLINE; SUCROSE; STARCH, CORN; ALPHA-TOCOPHEROL ACETATE; HYPROMELLOSES; FD&C BLUE NO. 1; FD&C YELLOW NO. 5; D&C RED NO. 33; FD&C RED NO. 4

Active Ingredient:
Ethyl Alcohol 62%

Purpose Antiseptic

Warnings:For external use only.

Flammable. Keep away from fire or flame.

Stop use and ask for a doctor if irritation or rash appears and lasts.

Keep out of reach of children. If swallowed, get medical help or contact a doctor right away.

Directions:
Pump as needed into your palms to cover hands. Rub hands together briskly until dry. Children under 6 years old should be supervised when using this product.

INACTIVE INGREDIENT

Inactive Ingredients: Water, Aloe Barbadensis Leaf Juice, Glycerin, Propylene Glycol, Fragrance, Carbomer, Aminomethyl Propanol, Lactose, Microcrystalline Cellulose, Sucrose, Zea Mays (corn) Starch, Ultramarine Blue CI 77007, Tocopheryl Acetate, Hydroxpropyl Methyl Cellulose, FD&C Blue No.1, FD&C Yellow No.5, FD&C Red No.33, FD&C Red No.4.

Other Information: Store below 118 F.

INDICATIONS AND USAGE

UseTo help reduce bacteria on the skin